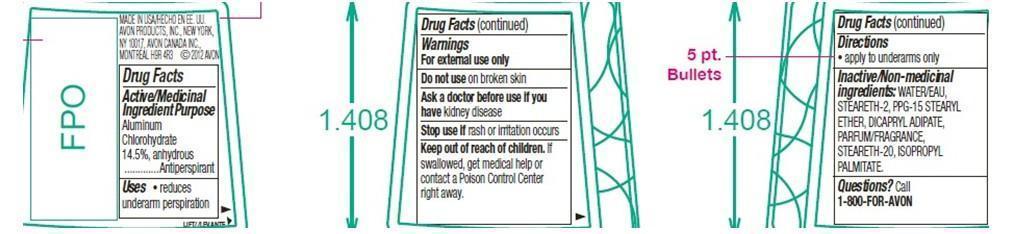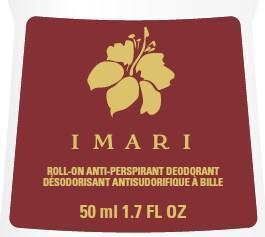 DRUG LABEL: Imari
NDC: 10096-9475 | Form: GEL
Manufacturer: The Avon Company
Category: otc | Type: HUMAN OTC DRUG LABEL
Date: 20210503

ACTIVE INGREDIENTS: ALUMINUM CHLOROHYDRATE 145 mg/1 mL
INACTIVE INGREDIENTS: WATER

Imari Anti-Perspirant Roll-on Deodorant

Active ingredient

Aluminum Chlorohydrate 14.5%, anhydrous......................

Uses

- reduces underarm perspiration

Warnings

For external use only

Do not use on broken skin

Ask a doctor before use if you have kidney disease

Stop use if rash or irritation occurs

Keep out of reach of children. If swallowed, get medical help or contact a Poison Control Center right away.

Directions

- apply to underarms only

INACTIVE INGREDIENT

Inactive ingredients: WATER/EAU, STEARETH-2, PPG-15 STEARYL ETHER, DICAPRYL ADIPATE, PARFUM/FRAGRANCE, STEARETH-20, ISOPROPYL PALMITATE

Questions?Call 1-800-FOR-AVON